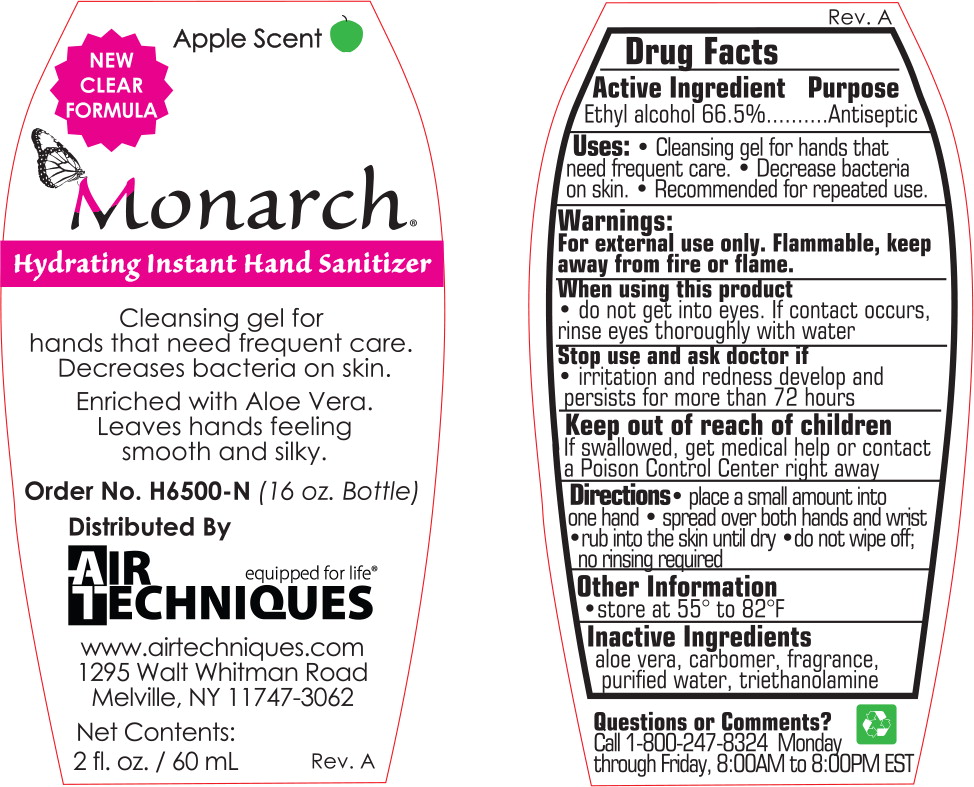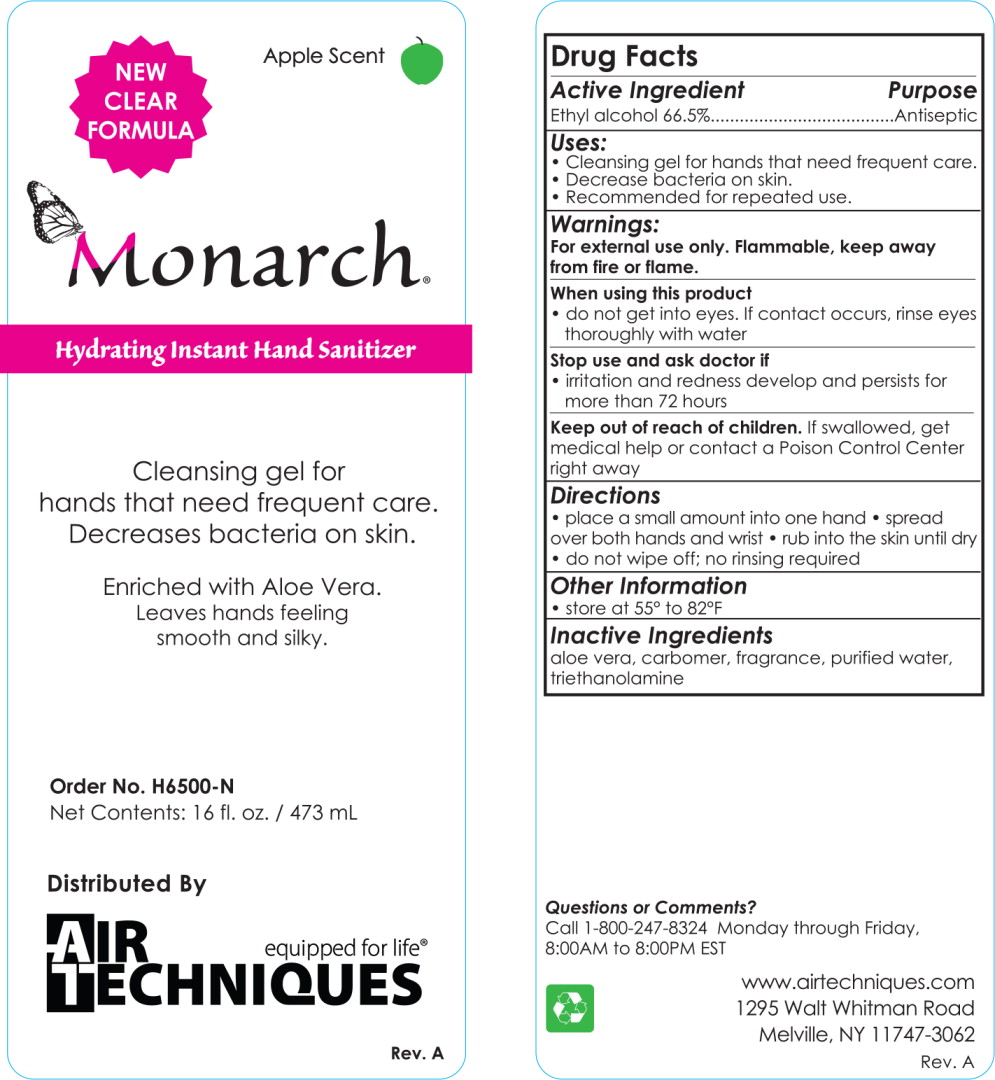 DRUG LABEL: Instant Hand Sanitizer
NDC: 69965-8111 | Form: GEL
Manufacturer: Air Techniques
Category: otc | Type: HUMAN OTC DRUG LABEL
Date: 20150710

ACTIVE INGREDIENTS: alcohol 700 mg/1000 mL
INACTIVE INGREDIENTS: aloe; water; trolamine

Drug Facts

Active Ingredient

Ethyl alcohol 66.5%

Purpose

Antiseptic

Uses:

- Cleansing gel for hands that need frequent care.
- Decrease bacteria on skin.
- Recommended for repeated use.

Warnings:

For external use only. Flammable, keep away from fire or flame.

When using this product

- do not get into eyes. If contact occurs, rinse eyes thoroughly with water

Stop use and ask doctor if

- irritation and redness develop and persists for more than 72 hours

Keep out of reach of children. If swallowed, get medical help or contact a Poison Control Center right away

Directions

- place a small amount into one hand
- spread over both hands and wrist
- rub into the skin until dry
- do not wipe off; no rinsing required

Other Information

- store at 55° to 82°F

Inactive Ingredients

aloe vera, carbomer, fragrance, purified water, triethanolamine

Principal Display Panel - 2 fl. oz. Label

Apple Scent

NEW CLEAR FORMULA

Monarch®

Hydrating Instant Hand Sanitizer

Cleansing gel for
hands that need frequent care.
Decreases bacteria on skin.

Enriched with Aloe Vera.
Leaves hands feeling
smooth and silky.

Order No. H6500-N (16 oz. Bottle)

Distributed By

AIR TECHNIQUES

equipped for life®

www.airtechniques.com

1295 Welt Whitman Road

Melville, NY 11747-3062

Net Contents:

2 fl. oz. / 60mL

Rev. A

Principal Display Panel - 16 fl. oz. Label

Apple Scent

NEW CLEAR FORMULA

Monarch®

Hydrating Instant Hand Sanitizer

Cleansing gel for
hands that need frequent care.
Decreases bacteria on skin.

Enriched with Aloe Vera.
Leaves hands feeling
smooth and silky.

Order No. H6500-N

Net Contents: 16 fl. oz. / 473 mL

Distributed By

AIR TECHNIQUES

equipped for life®

Rev. A